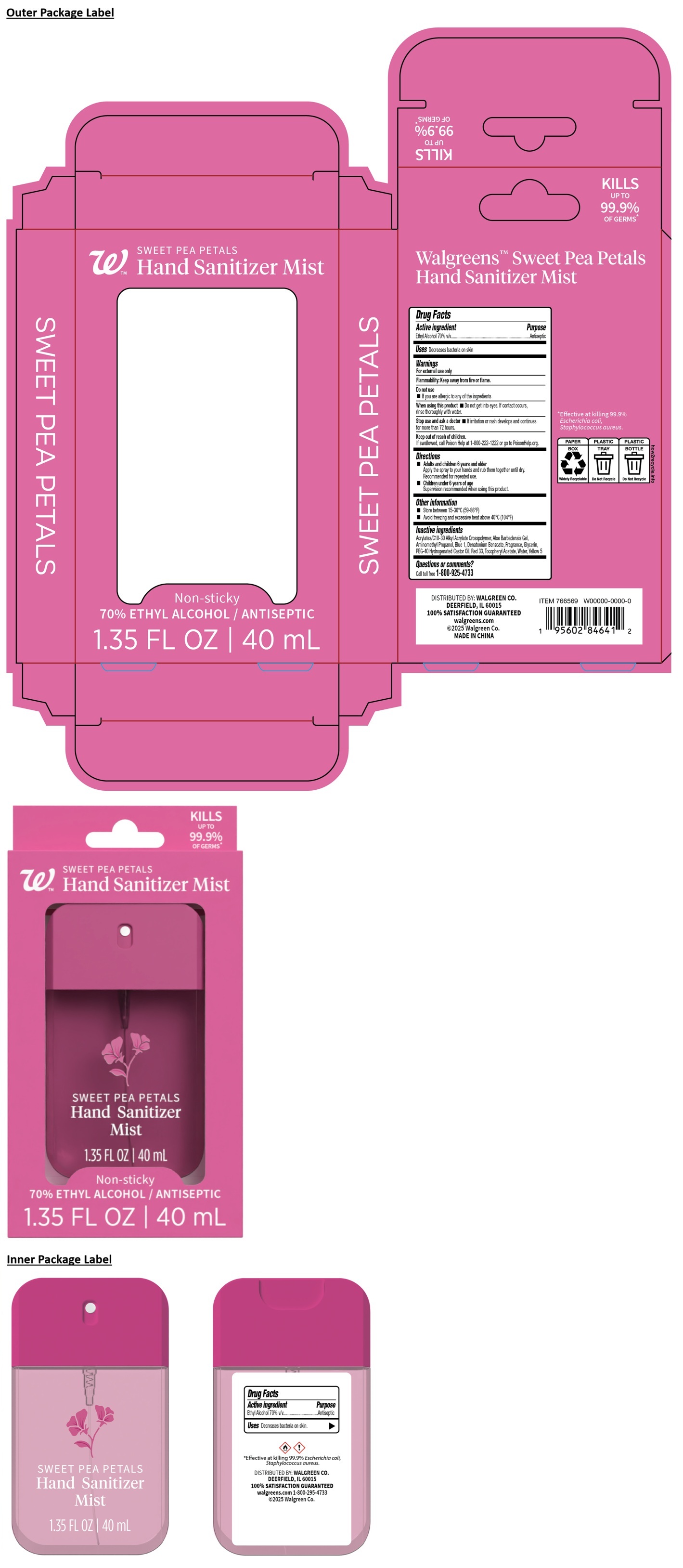 DRUG LABEL: Walgreens SWEET PEA PETALS Hand Sanitizer Mist
NDC: 0363-5192 | Form: SPRAY
Manufacturer: Walgreen Co.
Category: otc | Type: HUMAN OTC DRUG LABEL
Date: 20260121

ACTIVE INGREDIENTS: ALCOHOL 70 mL/100 mL
INACTIVE INGREDIENTS: ACRYLATES/C10-30 ALKYL ACRYLATE CROSSPOLYMER (60000 MPA.S); ALOE VERA LEAF; AMINOMETHYLPROPANOL; FD&C BLUE NO. 1; DENATONIUM BENZOATE; GLYCERIN; POLYOXYL 40 HYDROGENATED CASTOR OIL; D&C RED NO. 33; .ALPHA.-TOCOPHEROL ACETATE; WATER; FD&C YELLOW NO. 5

Walgreens™ Sweat Pea Petals Hand Sanitizer Mist

Active ingredient

Ethyl Alcohol 70% v/v

Purpose

Antiseptic

Uses

Decreases bacteria on skin

Warnings

For external use only

Flammability: Keep away from fire or flame.

Do not use
• If you are allergic to any of the ingredients

When using this product • Do not get into eyes. If contact occurs, rinse thoroughly with water.

Stop use and ask a doctor • If irritation or rash develops and continues for more than 72 hours.

Keep out of reach of children.
If swallowed, call Poison Help at 1-800-222-1222 or go to PoisonHelp.org.

Directions

• Adults and children 6 years and older
Apply the spray to your hands and rub them together until dry.
Recommended for repeated use.

• Children under 6 years of age
Supervision recommended when using this product.

Other information

• Store between 15-30°C (59-86°F)
• Avoid freezing and excessive heat above 40°C (104°F)

Inactive ingredients

Acrylates/C10-30 Alkyl Acrylate Crosspolymer, Aloe Barbadensis Gel, Aminomethyl Propanol, Blue 1, Denatonium Benzoate, Fragrance, Glycerin, PEG-40 Hydrogenated Castor Oil, Red 33, Tocopheryl Acetate, Water, Yellow 5

Questions or comments?

Call toll free 1-800-925-4733

Non-sticky

KILLS UP TO 99.9% OF GERMS*

DISTRIBUTED BY: WALGREEN CO.
DEERFIELD, IL 60015
100% SATISFACTION GUARANTEED

walgreens.com
©2025 Walgreen Co.
MADE IN CHINA

*Effective at killing 99.9% Escherichia coli, Staphylococcus aureus.